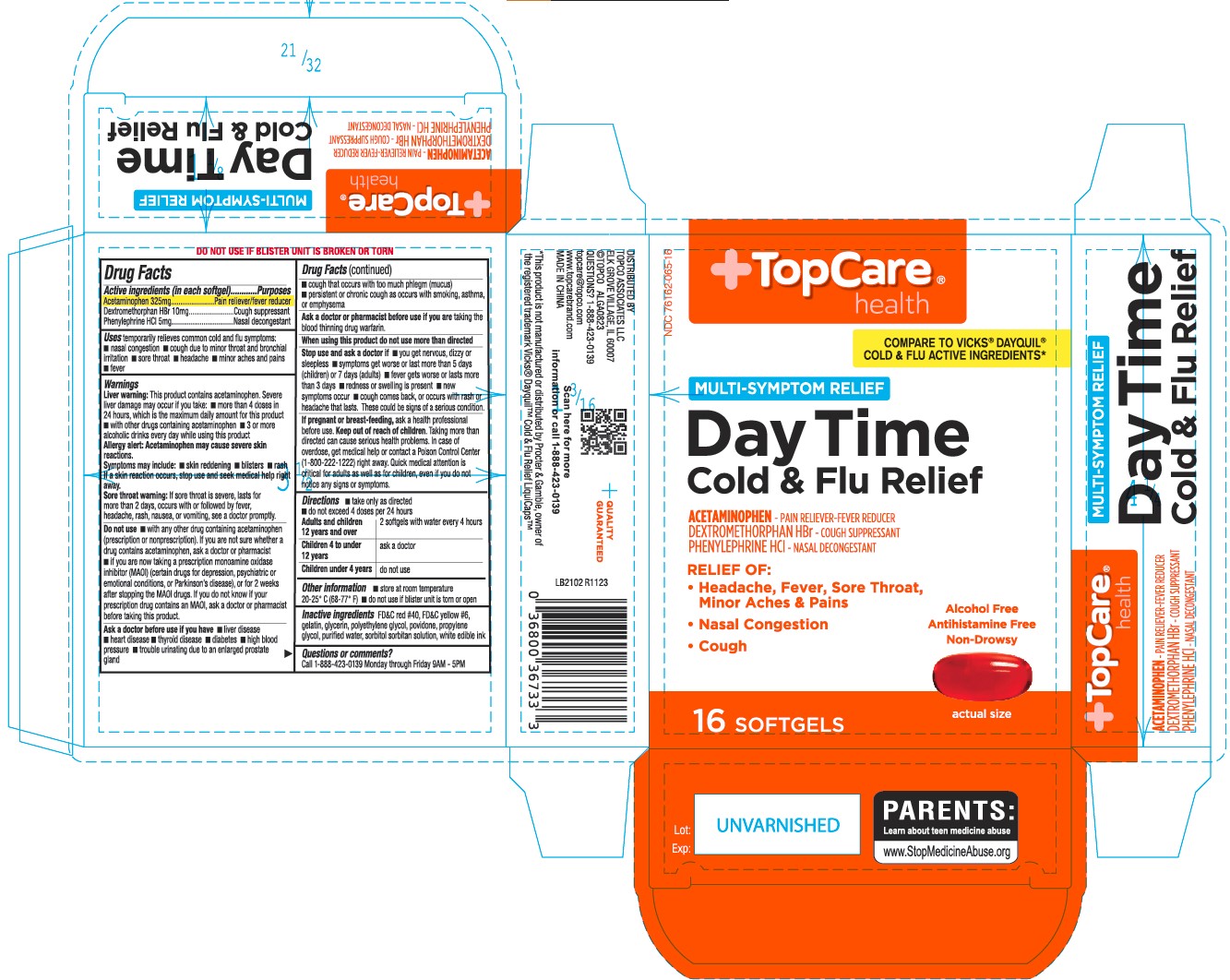 DRUG LABEL: Daytime Cold and Flu Relief
NDC: 76162-065 | Form: CAPSULE, LIQUID FILLED
Manufacturer: TopCo Associates, LLC
Category: otc | Type: HUMAN OTC DRUG LABEL
Date: 20231031

ACTIVE INGREDIENTS: ACETAMINOPHEN 325 mg/1 1; DEXTROMETHORPHAN HYDROBROMIDE 10 mg/1 1; PHENYLEPHRINE HYDROCHLORIDE 5 mg/1 1
INACTIVE INGREDIENTS: FD&C RED NO. 40; FD&C YELLOW NO. 6; GELATIN; GLYCERIN; POLYETHYLENE GLYCOL, UNSPECIFIED; POVIDONE; PROPYLENE GLYCOL; WATER; SORBITOL SOLUTION

417 - Daytime Cold and Flu Relief

Active ingredient(s)

Acetaminophen 325mg

Dextromethorphan HBr 10mg

Phenylephrine HCl 5mg

Purpose

Pain reliever/fever reducer

Cough suppressant

Nasal decongestant

Use(s)

- temporarily relieves common cold/flu symptoms:
- • nasal congestion
- • cough due to minor throat & bronchial irritation
- • sore throat
- • headache
- • minor aches & pains
- • fever

Warnings

Liver warning: This product contains acetaminophen.
Severe liver damage may occur if you take:
• more than 4 doses in 24 hrs, which is the maximum daily amount for this product
• with other drugs containing acetaminophen
• 3 or more alcoholic drinks every day while using this product

Allergy Alert: Acetaminophen may cause severe skin reactions.
Symptoms may include: • skin reddening • blisters • rash
If a skin reaction occurs, stop use and seek medical help right away.

Sore throat warning: If sore throat is severe, persists for more than 2 days,
occurs with or is followed by fever, headache, rash, nausea, or vomiting,
consult a doctor promptly.

Do not use

- with any other drug containing acetaminophen
  (prescription or nonprescription). If you are not sure whether a
  drug contains acetaminophen, ask a doctor or pharmacist
- if you are now taking a prescription monoamine oxidase
  inhibitor (MAOI) (certain drugs for depression, psychiatric or
  emotional conditions, or Parkinson’s disease), or for 2 weeks
  after stopping the MAOI drugs. If you do not know if your
  prescription drug contains an MAOI, ask a doctor or pharmacist
  before taking this product.

Ask a doctor before use if

• liver disease • heart disease • thyroid disease • diabetes • high blood pressure
• trouble urinating due to an enlarged prostate gland • cough that occurs
with too much phlegm (mucus) • persistent or chronic cough as occurs
with smoking, asthma, or emphysema

Ask a doctor or pharmacist before use if

taking the blood thinning drug warfarin.

When using this product

do not use more than directed

Stop use and ask a doctor if

• you get nervous, dizzy or sleepless
• symptoms get worse or last more than 5 days (children) or 7 days (adults)
• fever gets worse or lasts more than 3 days
• redness or swelling is present •new symptoms occur
• cough comes back, or occurs with rash or headache that lasts.
These could be signs of a serious condition.

If pregnant or breastfeeding,

ask a health professional before use.

Keep out of reach of children

Taking more than directed can cause serious health problems. In case of
overdose, get medical help or contact a Poison Control Center
(1-800-222-1222) right away. Quick medical attention is
critical for adults as well as for children, even if you do not
notice any signs or symptoms.

Directions

- Take only as directed

- Do not exceed 4 doses in 24 hours

adults and children 12 years & over: 2 softgels with water every 4 hours

children 4 to under 12 years: ask a doctor

children under 4 years: do not use

Other information

- store at room temperature 20-25 °C (68-77° F)

- do not use if blister unit is torn or open

Inactive ingredients

FD&C red #40, FD&C yellow #6,
gelatin, glycerin, polyethylene glycol, povidone, propylene
glycol, purified water, sorbitol sorbitan solution, white edible ink

Questions/Comments

Call 1-888-952-0050 Monday through Friday 9AM - 5PM

Principal Display Panel

Daytime Cold and Flu